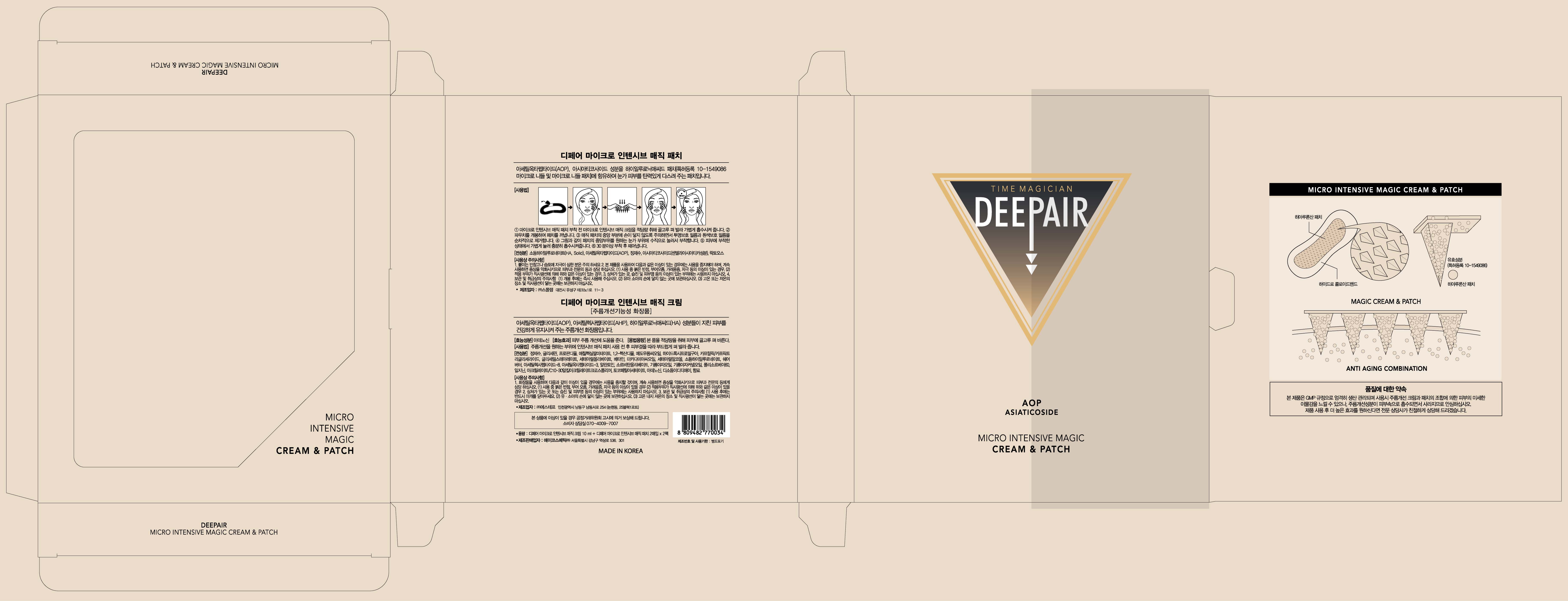 DRUG LABEL: DEEPAIR MICRO INTENSIVE MAGIC
NDC: 70961-0001 | Form: PATCH
Manufacturer: Acosmetic. Co.ltd
Category: otc | Type: HUMAN OTC DRUG LABEL
Date: 20160918

ACTIVE INGREDIENTS: HYALURONATE SODIUM 6.1 g/100 mg
INACTIVE INGREDIENTS: WATER; MADECASSOSIDE; LACTOSE

Drug Facts

ACTIVE INGREDIENT

Sodium Hyaluronate

INACTIVE INGREDIENT

Water, Acetyl Octapeptide-3, Caprylyl Glycol, Madecassoside, Lactose

PURPOSE

Skin Protectant

keep out of reach of the children

INDICATIONS AND USAGE

1. Apply DEEPAIR MICRO INTENSIVE MAGIC CREAM before attaching the patches.
2. Open the pouch.
3. Remove the films.
4. Attach the patches around the eye areas.
5. Pat firm.
6. Leave it for more than 30 minutes.

WARNINGS

1. If the following symptoms occur after product use, stop using the product immediately and consult a dermatologist (continuous use can exacerbate the symptoms).
1) Occurrence of red spots, swelling, itchiness, and other skin irritation
2) If the symptoms above occur after the application area is exposed to direct sunlight
2. Do not use on open wounds, eczema, and other skin irritations
3. Precaution for Storage and Handling
1) Close the lid after use
2) Keep out of reach of infants and children
3) Do not to store in a place with high/low temperature and exposed to direct sunlight

4. Use as avoiding eye areas.

DOSAGE AND ADMINISTRATION

for external use only